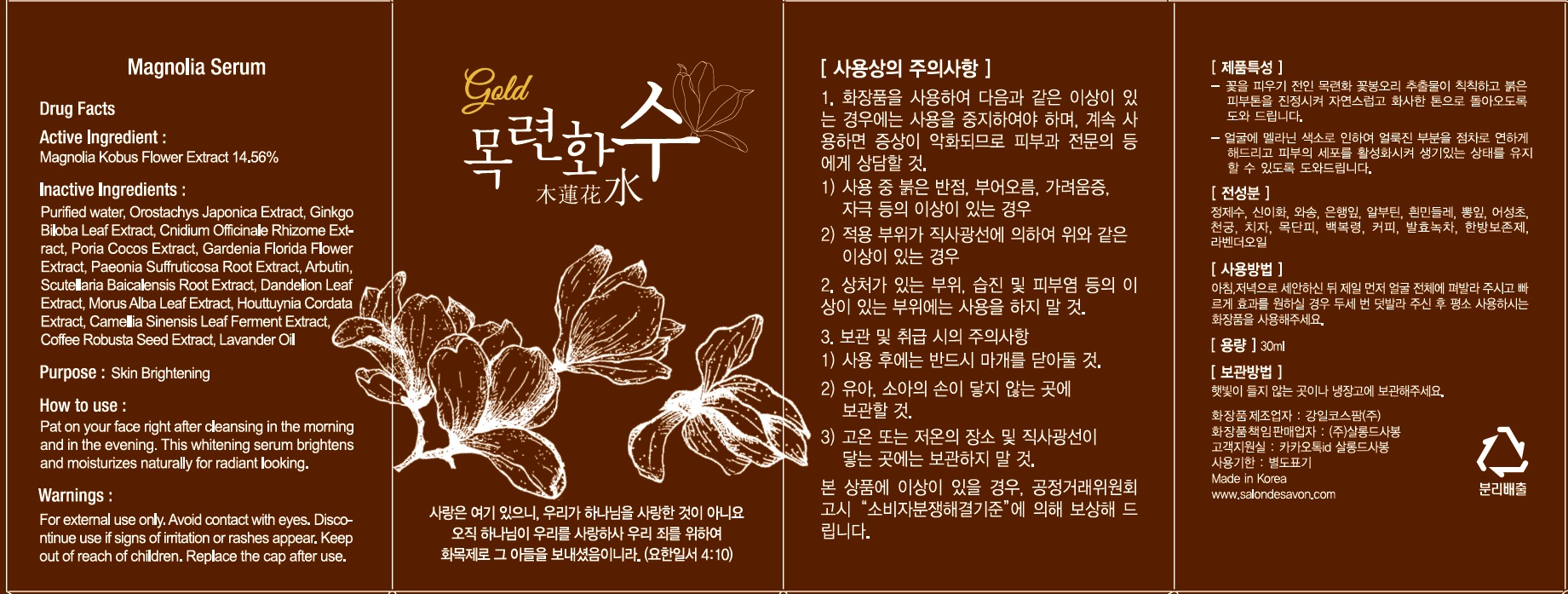 DRUG LABEL: Magnolia Serum
NDC: 81355-100 | Form: LIQUID
Manufacturer: Grace & Truth Co.,Ltd.
Category: otc | Type: HUMAN OTC DRUG LABEL
Date: 20201224

ACTIVE INGREDIENTS: MAGNOLIA KOBUS FLOWERING TOP 4.36 g/30 mL
INACTIVE INGREDIENTS: Water; Arbutin

ACTIVE INGREDIENT

Magnolia Kobus Flower Extract 14.56%

INACTIVE INGREDIENTS

Purified water, Orostachys Japonica Extract, Ginkgo Biloba Leaf Extract, Cnidium Officinale Rhizome Extract, Poria Cocos Extract, Gardenia Florida Flower Extract, Paeonia Suffruticosa Root Extract, Dandelion Leaf Extract, Morus Alba Leaf Extract, Houttuynia Cordata Extract, Arbutin, Scutellaria Baicalensis Root Extract, Camellia Sinensis Leaf Ferment Extract, Coffee Robusta Seed Extract, Lavander Oil

PURPOSE

Skin Brightening

WARNINGS

For external use only. Avoid contact with eyes. Discontinue use if signs of irritation or rashes appear. Keep out of reach of children. Replace the cap after use.

KEEP OUT OF REACH OF CHILDREN

Uses

This whitening serum brightens and monetarizes naturally for radiant looking.

Directions

Pat on your face right after cleansing in the morning and in the evening.